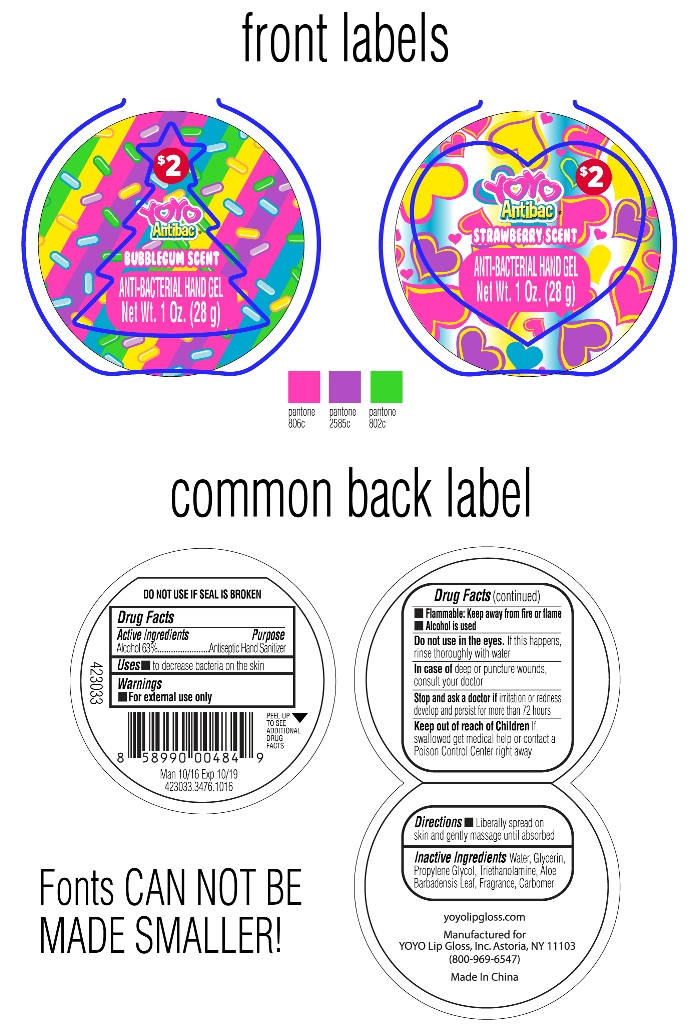 DRUG LABEL: Hand sanitizer
NDC: 70939-001 | Form: SWAB
Manufacturer: Dongguang Shuoguo Silicone Products Co., Ltd.
Category: otc | Type: HUMAN OTC DRUG LABEL
Date: 20200201

ACTIVE INGREDIENTS: ALCOHOL 63 mL/100 mL
INACTIVE INGREDIENTS: PROPYLENE GLYCOL; WATER; GLYCERIN; CARBOMER 934; TROLAMINE

ASSURED ANTIBACTERIAL WET WIPES 70939-001

Active ingredient

Alcohol 63%

Purpose

Antiseptic Hand Sanitizer

Use

to decrease bacteria on the skin

Warnings

For external use only

Flammable: Keep away from fire or flame

Alcohol is used

Do not use in the eyes. If this happens, rinse thoroughly with water.

In case of deep or puncture wounds, consult your doctor

Stop use and ask a doctor if irritation or redness develops and persists for more than 72 hours

Keep out of reach of children

if swallowed
get medical help or contact a Poison Control Center right away.

Directions

Liberally spray on skin and gently massage until absorbed

INACTIVE INGREDIENT

Glycerin, Propylene Glycol, Triethanolamine, Aloe Barbadenis Leaf, Fragrance, Carbomer